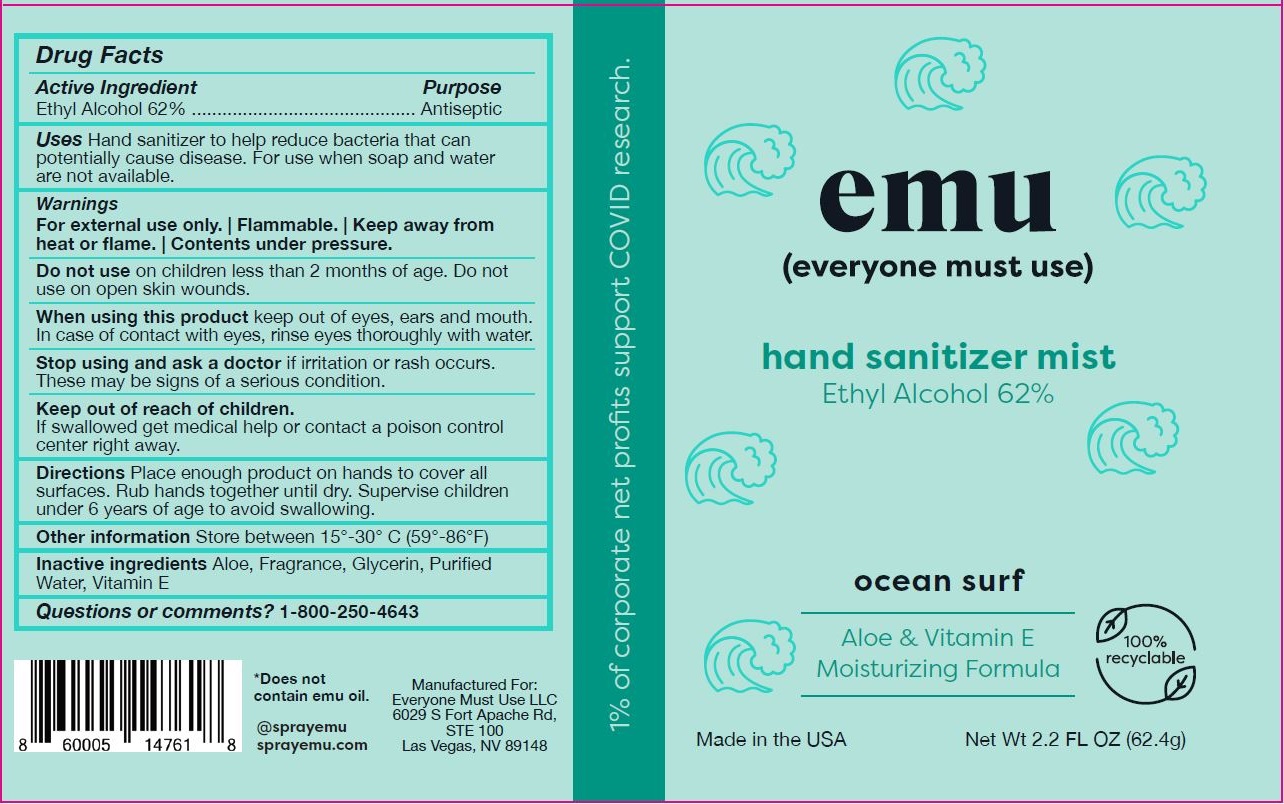 DRUG LABEL: EMU Hand Sanitizer Mist Ocean Surf
NDC: 80464-1002 | Form: SPRAY
Manufacturer: EVERYONE MUST USE, LLC
Category: otc | Type: HUMAN OTC DRUG LABEL
Date: 20231222

ACTIVE INGREDIENTS: ALCOHOL 0.62 g/1 g
INACTIVE INGREDIENTS: GLYCERIN; ALOE; WATER; ALPHA-TOCOPHEROL ACETATE

EMU Hand Sanitizer Mist Ethyl Alcohol 62% Ocean Surf

Purpose

Antiseptic, Hand Sanitizer

Drug Facts

Active Ingredient

Active Ingredient | Purpose
Alcohol 80% v/v. | Antiseptic

Uses

Hand sanitizer to help reduce bacteria that potentially can cause disease. For use when soap and water are not available.

Warnings

For external use only. | Flammable. | Keep away from heat or flame. | Contents under pressure.

Do not use on children less than 2 months of age. Do not use on open skin wounds.

When using this product keep out of eyes, ears, and mouth. In case of contact with eyes, rinse eyes thoroughly with water.

STOP USE

Stop using and ask a doctor if irritation or rash occurs. These may be signs of a serious condition.

Keep out of reach of children. If swallowed, get medical help or contact a poison control center right away.

Directions

Place enough product on hands to cover all surfaces. Rub hands together until dry. Supervise children under 6 years of age to avoid swallowing.

Other information

Store between 15°-30° C (59°-86°F)

Inactive ingredients

Aloe, Fragrance, Glycerin, Purified Water, Vitamin E

Questions or comments?

1-800-250-4643

Package Label - Principal Display Panel

Net Wt 2.2 FL OZ (62.4g) NDC: 80464-1002-1